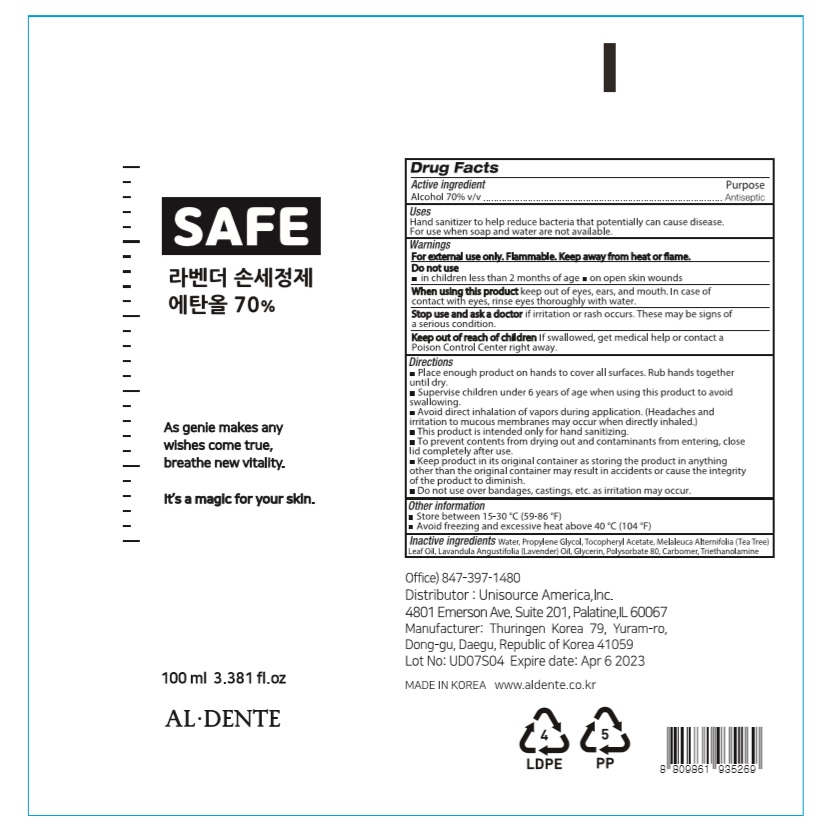 DRUG LABEL: Lavender Hand Sanitizer
NDC: 74864-0170 | Form: GEL
Manufacturer: THURINGEN KOREA Co., Ltd.
Category: otc | Type: HUMAN OTC DRUG LABEL
Date: 20200407

ACTIVE INGREDIENTS: ALCOHOL 70 mL/100 mL
INACTIVE INGREDIENTS: TEA TREE OIL; LAVENDER OIL; POLYSORBATE 80; GLYCERIN; CARBOMER HOMOPOLYMER, UNSPECIFIED TYPE; WATER; .ALPHA.-TOCOPHEROL ACETATE; PROPYLENE GLYCOL; TROLAMINE

Lavender Hand Sanitizer 100 ml : 74864-0170